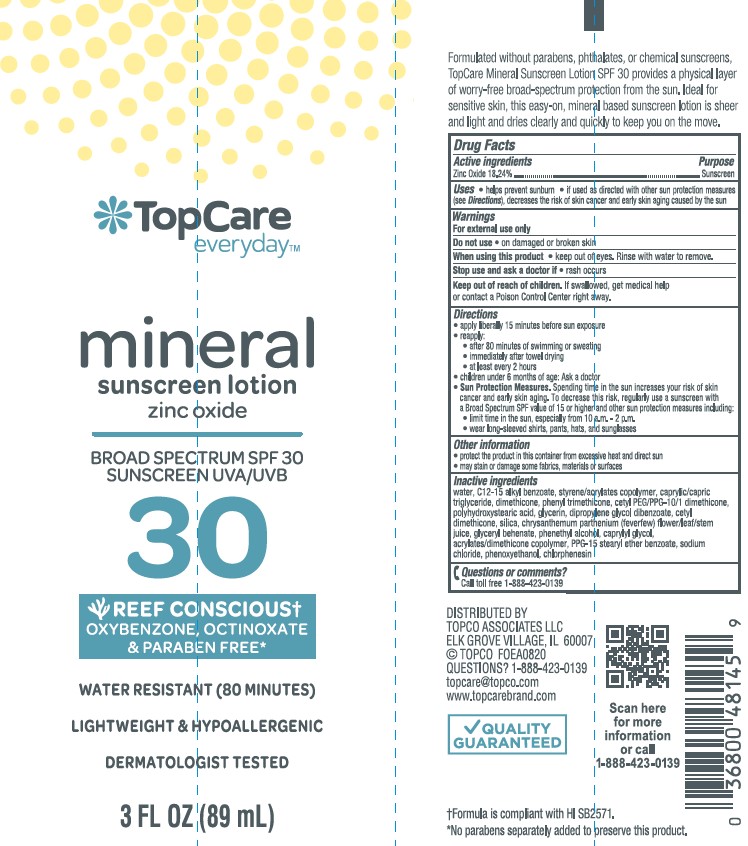 DRUG LABEL: TopCare Everyday Mineral Sunscreen Zinc Oxide SPF 30
NDC: 36800-260 | Form: LOTION
Manufacturer: TOPCO ASSOCIATES LLC
Category: otc | Type: HUMAN OTC DRUG LABEL
Date: 20241015

ACTIVE INGREDIENTS: ZINC OXIDE 182.4 mg/1 mL
INACTIVE INGREDIENTS: WATER; ALKYL (C12-15) BENZOATE; MEDIUM-CHAIN TRIGLYCERIDES; DIPROPYLENE GLYCOL DIBENZOATE; PHENYL TRIMETHICONE; CETYL PEG/PPG-10/1 DIMETHICONE (HLB 5); DIMETHICONE; POLYHYDROXYSTEARIC ACID (2300 MW); GLYCERIN; PPG-15 STEARYL ETHER BENZOATE; CETYL DIMETHICONE 25; SILICON DIOXIDE; 2-ETHYLHEXYL ACRYLATE, METHACRYLATE, METHYL METHACRYLATE, OR BUTYL METHACRYLATE/HYDROXYPROPYL DIMETHICONE COPOLYMER (30000-300000 MW); GLYCERYL MONOBEHENATE; PHENYLETHYL ALCOHOL; CAPRYLYL GLYCOL; SODIUM CHLORIDE; PHENOXYETHANOL; CHLORPHENESIN; TANACETUM PARTHENIUM FLOWER

TopCare Everyday Mineral Sunscreen Lotion Zinc Oxide SPF 30

Active ingredients

Zinc Oxide 18.24%

Purpose

Sunscreen

Uses

• helps prevent sunburn • if used as directed with other sun protection measures (see Directions), decreases the risk of skin cancer and early skin aging caused by the sun

Warnings

For external use only

Do not use

• on damaged or broken skin

When using this product

• keep out of eyes. Rinse with water to remove.

Stop use and ask a doctor if

- rash occurs

Keep out of reach of children.

If swallowed, get medical help or contact a Poison Control Center right away.

Directions

• apply liberally 15 minutes before sun exposure

• reapply:

• after 80 minutes of swimming or sweating

• immediately after towel drying

• at least every 2 hours

• children under 6 months of age: Ask a doctor

- Sun Protection Measures. Spending time in the sun increases your risk of skin cancer and early skin aging. To decrease this risk, regularly use a sunscreen with a Broad Spectrum SPF value of 15 or higher and other sun protection measures including:

• limit time in the sun, especially from 10 a.m. - 2 p.m.

• wear long-sleeved shirts, pants, hats, and sunglasses

Other information

• protect the product in this container from excessive heat and direct sun

• may stain or damage some fabrics, materials or surfaces

Inactive ingredients

water, C12-15 alkyl benzoate, styrene/acrylates copolymer, caprylic/capric triglyceride, dimethicone, phenyl trimethicone, cetyl PEG/PPG-10/1 dimethicone, polyhydroxystearic acid, glycerin, dipropylene glycol dibenzoate, cetyl dimethicone, silica, chrysanthemum parthenium (feverfew) flower/leaf/stem juice, glyceryl behenate, phenethyl alcohol, caprylyl glycol, acrylates/dimethicone crosspolymer, PPG-15 stearyl ether benzoate, sodium chloride, phenoxyethanol, chlorphenesin